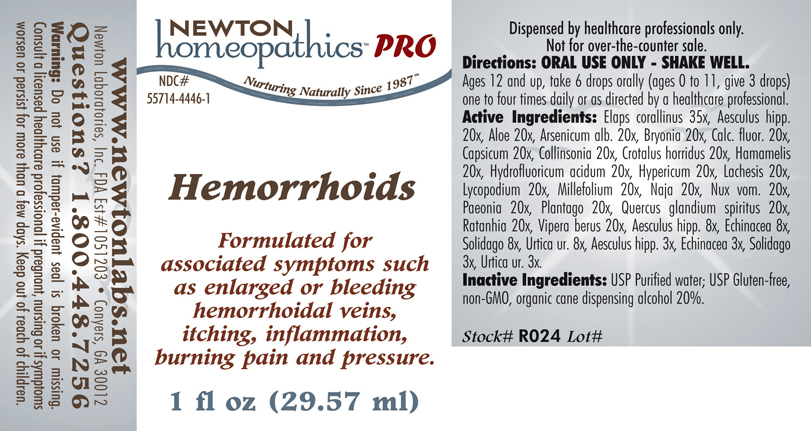 DRUG LABEL: Hemorrhoids 
NDC: 55714-4446 | Form: LIQUID
Manufacturer: Newton Laboratories, Inc.
Category: homeopathic | Type: HUMAN PRESCRIPTION DRUG LABEL
Date: 20110601

ACTIVE INGREDIENTS: Micrurus Corallinus Venom 35 [hp_X]/1 mL; Horse Chestnut 20 [hp_X]/1 mL; Aloe 20 [hp_X]/1 mL; Arsenic Trioxide 20 [hp_X]/1 mL; Bryonia Alba Root 20 [hp_X]/1 mL; Calcium Fluoride 20 [hp_X]/1 mL; Capsicum 20 [hp_X]/1 mL; Collinsonia Canadensis Root 20 [hp_X]/1 mL; Crotalus Horridus Horridus Venom 20 [hp_X]/1 mL; Hamamelis Virginiana Root Bark/stem Bark 20 [hp_X]/1 mL; Hydrofluoric Acid 20 [hp_X]/1 mL; Hypericum Perforatum 20 [hp_X]/1 mL; Lachesis Muta Venom 20 [hp_X]/1 mL; Lycopodium Clavatum Spore 20 [hp_X]/1 mL; Achillea Millefolium 20 [hp_X]/1 mL; Naja Naja Venom 20 [hp_X]/1 mL; Strychnos Nux-vomica Seed 20 [hp_X]/1 mL; Paeonia Officinalis Root 20 [hp_X]/1 mL; Plantago Major 20 [hp_X]/1 mL; Quercus Robur Nut 20 [hp_X]/1 mL; Krameria Lappacea Root 20 [hp_X]/1 mL; Vipera Berus Venom 20 [hp_X]/1 mL; Horse Chestnut 8 [hp_X]/1 mL; Echinacea, Unspecified 8 [hp_X]/1 mL; Solidago Virgaurea Flowering Top 8 [hp_X]/1 mL; Urtica Urens 8 [hp_X]/1 mL; Horse Chestnut 3 [hp_X]/1 mL; Echinacea, Unspecified 3 [hp_X]/1 mL; Solidago Virgaurea Flowering Top 3 [hp_X]/1 mL; Urtica Urens 3 [hp_X]/1 mL
INACTIVE INGREDIENTS: Alcohol

Hemorrhoids

PRODUCT NAME & INDICATIONS SECTION

HEMORRHOIDS Formulated for associated symptoms such as enlarged or bleeding hemorrhoidal veins, itching, inflammation, burning pain and pressure.

DIRECTION SECTION

Directions: ORAL USE ONLY - SHAKE WELL. Ages 12 and up, take 6 drops orally (ages 0 to 11, give 3 drops) one to four times daily or as directed by a healthcare professional.

ACTIVE INGREDIENT SECTION

Elaps corallinus 35x, Aesculus hipp. 20x, Aloe 20x, Arsenicum alb. 20x, Bryonia 20x, Calc. fluor. 20x, Capsicum 20x, Collinsonia 20x, Crotalus horridus 20x, Hamamelis 20x, Hydrofluoricum acidum 20x, Hypericum 20x, Lachesis 20x, Lycopodium 20x, Millefolium 20x, Naja 20x, Nux vom. 20x, Paeonia 20x, Plantago 20x, Quercus glandium spiritus 20x, Ratanhia 20x, Vipera berus 20x, Aesculus hipp 8x, Echinacea 8x, Solidago 8x, Urtica ur. 8x, Aesculus hipp. 3x, Echinacea 3x, Solidago 3x, Urtica ur. 3x.

PURPOSE SECTION

Formulated for associated symptoms such as enlarged or bleeding hemorrhoidal veins, itching, inflammation, burning pain and pressure.

INACTIVE INGREDIENT SECTION

Inactive Ingredients: USP Purified Water; USP Gluten-free, non-GMO, organic cane dispensing alcohol 20%.

QUESTIONS SECTION

www.newtonlabs.net Newton Laboratories, Inc. FDA Est # 1051203 - Conyers, GA 30012
Questions? 1.800.448.7256

WARNINGS? SECTION

Warning: Do not use if tamper - evident seal is broken or missing. Consult a licensed healthcare professional if pregnant, nursing or if symptoms worsen or persist for more than a few days. Keep out of reach of children.

OTC - PREGNANCY OR BREAST FEEDING SECTION

Consult a licensed healthcare professional if pregnant or nursing or if symptoms worsen or persist for more than a few days.

OTC - KEEP OUT OF REACH OF CHILDREN SECTION

Keep out of reach of children.